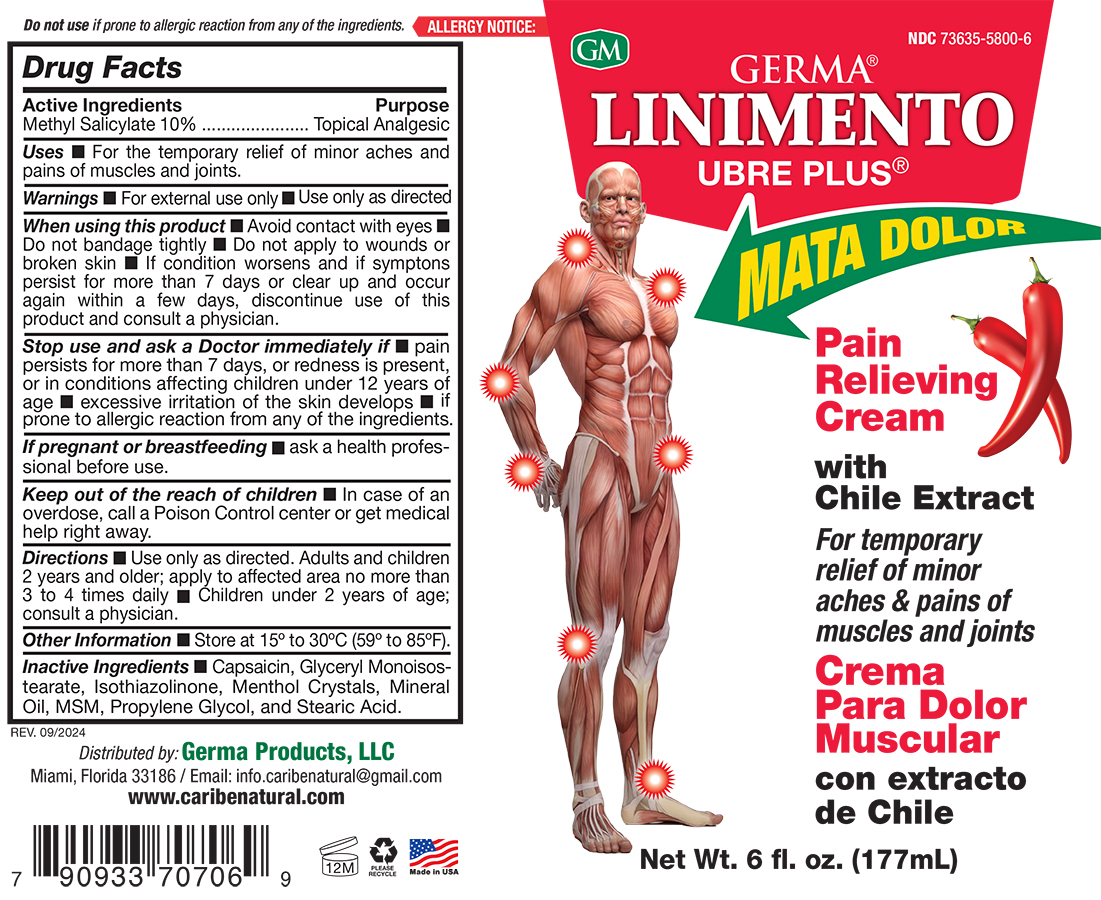 DRUG LABEL: Germa Linimento Ubre Plus
NDC: 73635-5800 | Form: OINTMENT
Manufacturer: Germa Products, LLC
Category: otc | Type: HUMAN OTC DRUG LABEL
Date: 20251024

ACTIVE INGREDIENTS: METHYL SALICYLATE 100 mg/1 mL
INACTIVE INGREDIENTS: CAPSAICIN; MENTHOL; GLYCERYL ISOSTEARATE; STEARIC ACID; MINERAL OIL; ISOTHIAZOLINONE; DIMETHYL SULFONE; PROPYLENE GLYCOL

Linimento Ubre Plus

Active Ingredient

Methyl Salicylate 10%

Uses

For the temporary relief of minor aches and pains of muscles and joints.

Purpose

Topical Analgesic

Warnings

For external use only ■ Use only as directed

Warnings

KEEP OUT OF THE REACH OF CHILDREN

In case of an overdose, call a Poison Control center or get medical help right away.

If pregnant or Breastfeeding

If pregnant or breast-feeding, ask a health professional before use.

Stop use and ask a Doctor immediately if

pain persists for more than 7 days, or redness is present, or in conditions affecting children under 12 years of age • excessive irritation of the skin develops • if prone to allergic reaction from any of the ingredients.

Other Information

Store at controlled room temperature 15-30ºC (59-86ºF)

Directions

Use only as directed. Adults and children 2 years and older; apply to the affected area no more than 3 to 4 times daily n Children under 2 years of age; consult a physician.

Inactive Ingredients

Capsaicin, Glyceryl Monoisostearate, Isothiazolinone, Menthol Crystals, Mineral Oil, MSM, Propylene Glycol, and Stearic Acid.

When Using this product

Avoid contact with eyes • Do not bandage tightly • Do not apply to wounds or broken skin • If the condition worsens and if symptoms persist for more than 7 days or clear up and occur again within a few days, discontinue use of this product and consult a physician.